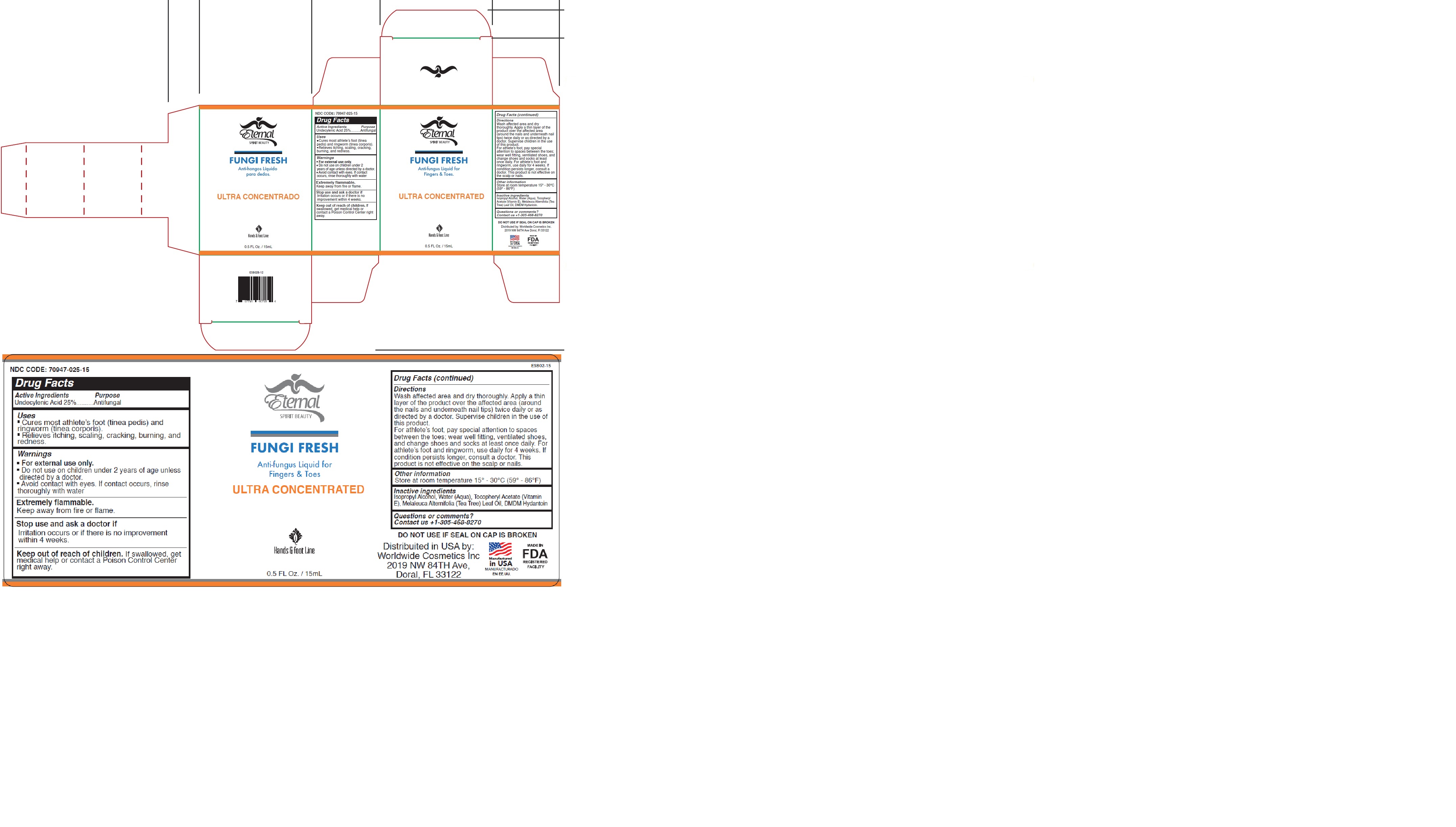 DRUG LABEL: ETERNAL SPIRIT BEAUTY FUNGI FRESH
NDC: 70947-025 | Form: LIQUID
Manufacturer: Worldwide Cosmetics, Inc
Category: otc | Type: HUMAN OTC DRUG LABEL
Date: 20231205

ACTIVE INGREDIENTS: UNDECYLENIC ACID 25 g/100 mL
INACTIVE INGREDIENTS: DMDM HYDANTOIN; .ALPHA.-TOCOPHEROL ACETATE, D-; ISOPROPYL ALCOHOL; MELALEUCA ALTERNIFOLIA LEAF; WATER

70947-025-15

ACTIVE INGREDIENT

Undecylenic Acid 25%

PURPOSE

Antifungal

USES:

• Cures most athlete’s foot (tinea pedis) and ringworm
(tinea corporis).
• Relieves itching, scaling, cracking, burning, and redness.

WARNINGS

.• For external use only.• Do not use on children under 2 years of age unless directed by a doctor.• Avoid contact with eyes. If contact occurs, rinse thoroughly with water

EXTREMELY FLAMMABLE

Keep away from fire or flame.

STOP USE

Irritation occurs or if there is no improvement within 4 weeks.

KEEP OUT OF REACH OF CHILDREN

If swallowed, get medical help or contact a Poison Control Center right away.

DIRECTIONS:

Shake well before using. Wash affected area and
dry thoroughly. Apply a thin layer of the product
over the affected area (around the nails and
underneath nail tips) twice daily or as directed by
a doctor. Supervise children in the use of this
product. For athlete’s foot, pay special attention
to spaces between the toes; wear well fitting,
ventilated shoes and change shoes and socks at
least once daily. For athlete’s foot and ringworm,
use daily for 4 weeks. If condition persists longer,
consult a doctor. This product is not effective on
the scalp or nails.

OTHER INFORMATION:

Store at room temperature 15° - 30°C (59° - 86°F)

INACTIVE INGREDIENT

Isopropyl Alcohol, Aqua, Tocopheryl Acetate, Melaleuca Alternifolia Leaf Oil, DMDM Hydantoin.

QUESTIONS OR COMMENTS?

Contact us +1-305-468-8270